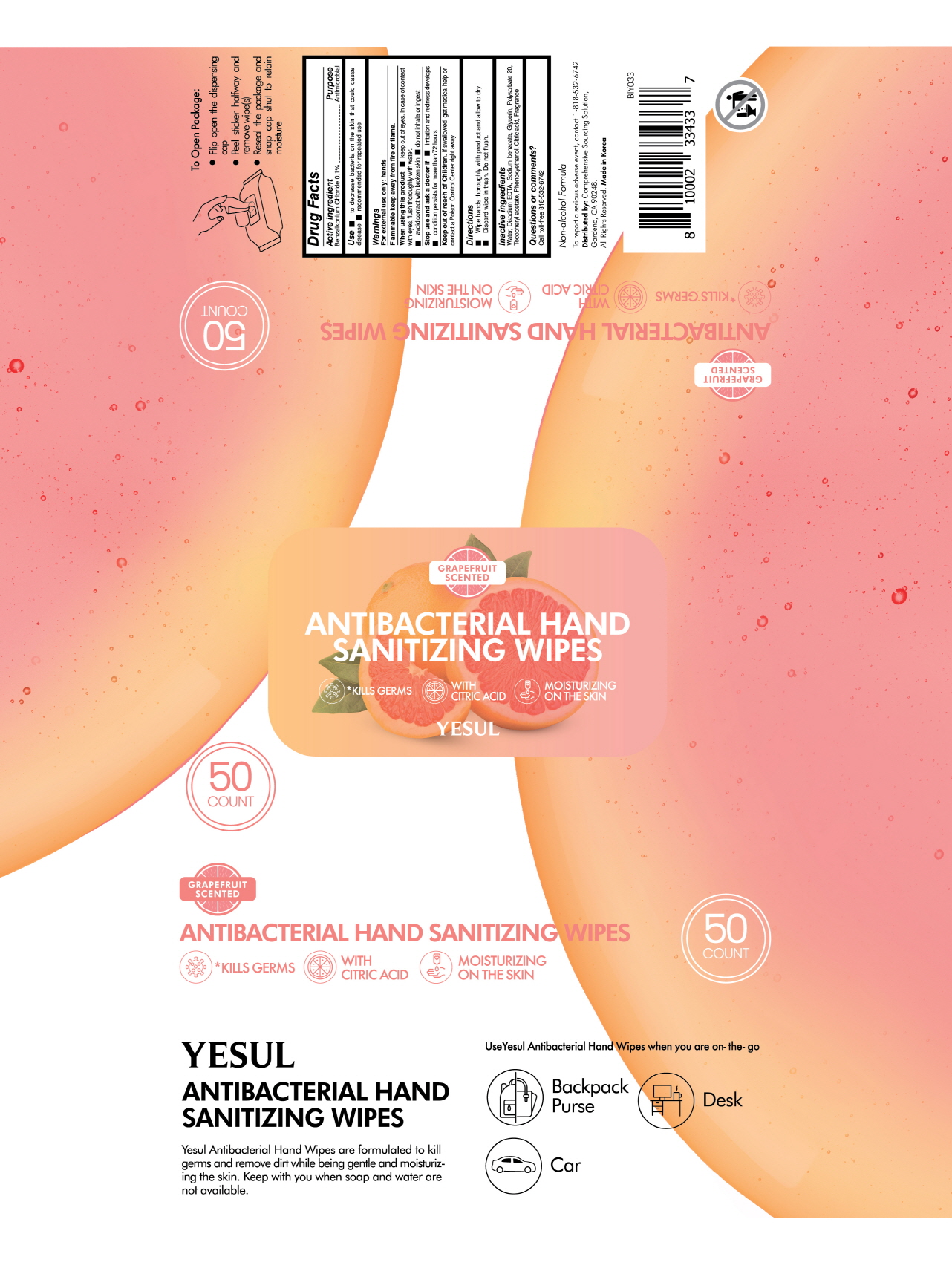 DRUG LABEL: YESUL ANTIBACTERIAL HAND SANITIZING WIPES
NDC: 76966-0016 | Form: CLOTH
Manufacturer: N Bridge Inc.
Category: otc | Type: HUMAN OTC DRUG LABEL
Date: 20200731

ACTIVE INGREDIENTS: BENZALKONIUM CHLORIDE 0.197 g/50 1
INACTIVE INGREDIENTS: PHENOXYETHANOL; EDETATE DISODIUM ANHYDROUS; SODIUM BENZOATE; WATER; CITRIC ACID MONOHYDRATE; GLYCERIN; POLYSORBATE 20; .ALPHA.-TOCOPHEROL ACETATE

ACTIVE INGREDIENT

benzalkonium chloride

INACTIVE INGREDIENT

water, disodium EDTA, sodium benzoate, glycerin, polysorbate 20, tocopheryl acetate, phenoxyethanol, citric acid

PURPOSE

Antiseptic

keep out of reach of the children

INDICATIONS AND USAGE

wet hands thoroughly with product and allow to dry without wiping

for children under 6, use only under adult supervision

not recommended for infants

WARNINGS

For external use only. Flammable. Keep away from heat or flame.

Do not use

- in children less than 2 months of age
- on open skin wounds

When using this product keep out of eyes, ears, and mouth. In case of contact with eyes, rinse thoroughly with water.

Stop use and ask a doctor if irritation or rash occurs. These may be signs of a serious condition.

Keep out of reach of children. If swallowed, get medical help or contact a Poison Control Center right away.

DOSAGE AND ADMINISTRATION

for external use only